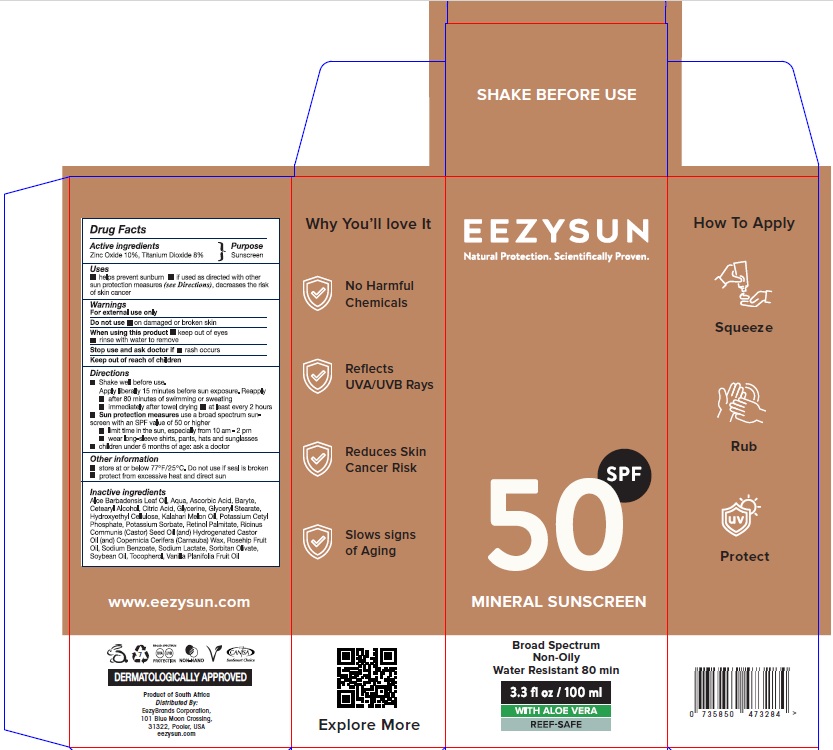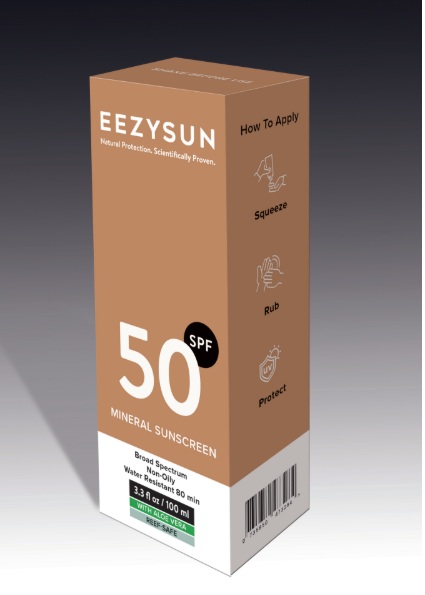 DRUG LABEL: Eezysun SPF 50 Adults
NDC: 70116-027 | Form: CREAM
Manufacturer: BIO EARTH MANUFACTURING (PTY) LTD
Category: otc | Type: HUMAN OTC DRUG LABEL
Date: 20250528

ACTIVE INGREDIENTS: TITANIUM DIOXIDE 8 g/100 mL; ZINC OXIDE 10 g/100 mL
INACTIVE INGREDIENTS: ALOE VERA LEAF POLYSACCHARIDES; WATER; ASCORBIC ACID; BARIUM SULFATE; CETOSTEARYL ALCOHOL; CITRIC ACID MONOHYDRATE; GLYCERIN; GLYCERYL MONOSTEARATE; HYDROXYETHYL CELLULOSE, UNSPECIFIED; CITRUS X LIMON FLOWERING TOP OIL; POTASSIUM CETYL PHOSPHATE; POTASSIUM SORBATE; VITAMIN A PALMITATE; CASTOR OIL; HYDROGENATED CASTOR OIL; CARNAUBA WAX; ROSA MOSCHATA OIL; SODIUM BENZOATE; SODIUM LACTATE; SORBITAN OLIVATE; SOYBEAN OIL; .ALPHA.-TOCOPHEROL ACETATE; VANILLA PLANIFOLIA OIL

Active ingredients

Zink Oxide 10 % & Titanium Dioxide 8 %

Purpose

Sunscreen

Uses

- helps prevent sunburn
- If used as directed with other sun protection measures (see Directions), decreases the risk of skin cancer

Warnings

- For external use only.
- Do not use: on damaged or broken skin.
- When using this product: keep out of the eyes, rinse with water to remove.
- Stop using this product if: Rash occurs

Directions

- Shake well before use.
- Apply liberally 15 minutes before sun exposure

Reapply

- after 80 minutes if swimming or sweating
- immediately after towel drying
- at least every two hours

Sun protection measures use a broad-spectrum sunscreen with an SPF value of 50 or higher

- limit time in the sun, especially from 10am - 2pm
- wear long-sleeve shirts, pants, hats, sunglasses
- Children under 6 months of age: ask a doctor

Other Information

- Store at or below 77⁰ F/25⁰C
- Do not use if seal is broken
- protect from excessive heat and direct sun

Inactive ingredients

Aloe Vera, Aqua, Ascorbic Acid, Barium Sulphate, Cetearyl Alcohol, Citric Acid, Glycerine, Glyceryl Stearate, Hydroxyethyl Cellulose, Citrullus Vulgaris (Kalahari Melon) Oil, Potassium Cetyl Phosphate, Potassium Sorbate, Retinol Palmitate, Ricinus Communis(Castor)Ceed Oil, Hydrogenated Castor Oil, Copernica Cerifera(Carnauba)Wax, Rosehip Fruit Oil, Sodium Benzoate, Sodium Lactate, Sorbitan Olivate, Soybean Oil, Tocopherol, Vanilla Planifolia Fruit Oil